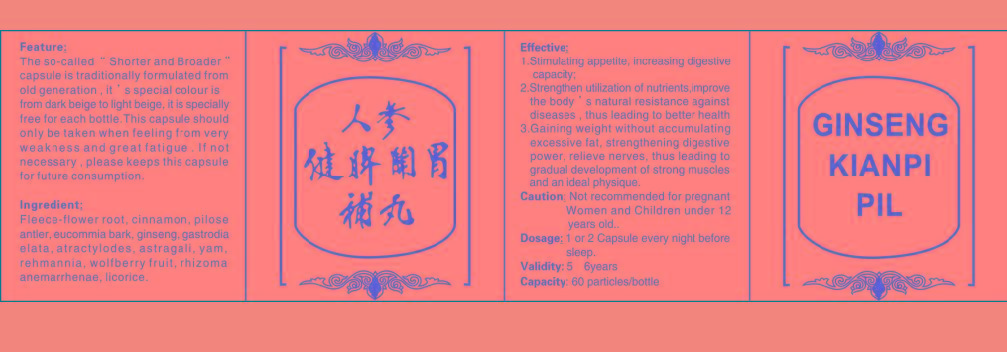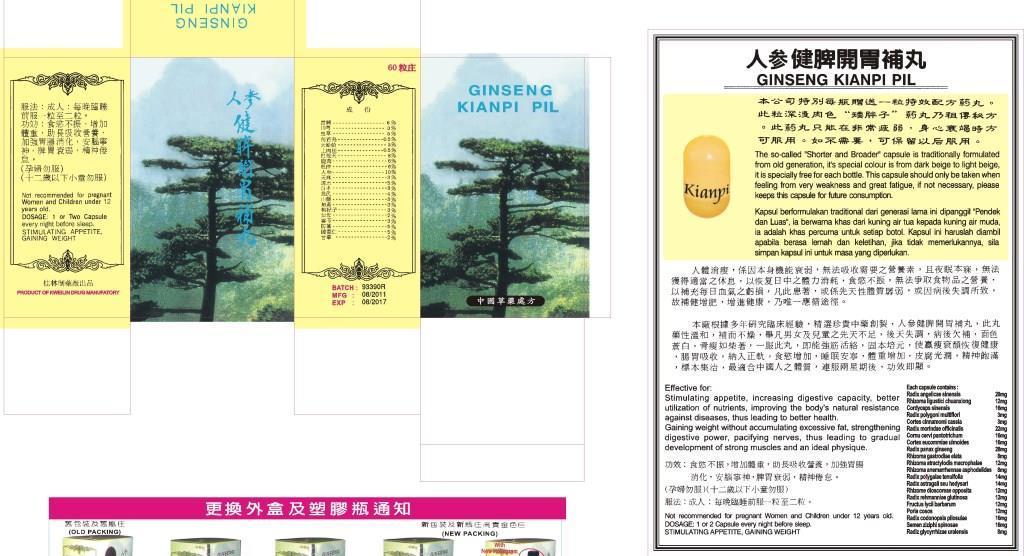 DRUG LABEL: GINSENG KIANPI PIL
NDC: 61551-0101 | Form: CAPSULE
Manufacturer: Guangzhou HanWindBeauty Commerce Co.,Ltd
Category: homeopathic | Type: HUMAN OTC DRUG LABEL
Date: 20140107

ACTIVE INGREDIENTS: ANGELICA SINENSIS WHOLE 20 mg/1 g; MORINDA OFFICINALIS WHOLE 22 mg/1 g; PANAX GINSENG ROOT OIL 28 mg/1 g
INACTIVE INGREDIENTS: STARCH, CORN 930 mg/1 g

Active ingredient

ANGELICA SINENSIS WHOLE: 20MG/Capsule

MORINDA OFFICINALIS WHOLE: 22MG/Capsule

PANAX GINSENG ROOT OIL: 28MG/Capsule

Purpose

Stimulating appetite, increasing digestive capacity;

Strengthen utilization of nutrients, improve the body’s natural resistance against diseases, thus leading to better health;

Gaining weight without accumulating excessive fat, strengthening digestive power, relieves nerves, thus leading to gradual development of strong muscles and an ideal physique.

Indications and usage

Indications:

Stimulating appetite, increasing digestive capacity;

Strengthen utilization of nutrients, improve the body’s natural resistance against diseases, thus leading to better health;

Gaining weight without accumulating excessive fat, strengthening digestive power, relieves nerves, thus leading to gradual development of strong muscles and an ideal physique.

Usage:

1 or 2 Capsule every night before sleep.

Dosage

1g/dosage.

Warnings

Not recommended for pregnant Women and Children under 12 years old.

Keep out of reach of children. If the product is swallowed, get medical help or contact a Poison Control Center right away.

Package label - Principal display panel

Package Label.jpg.

Container Label.jpg

Inactive ingredient

STARCH, CORN: 930MG/Capsule